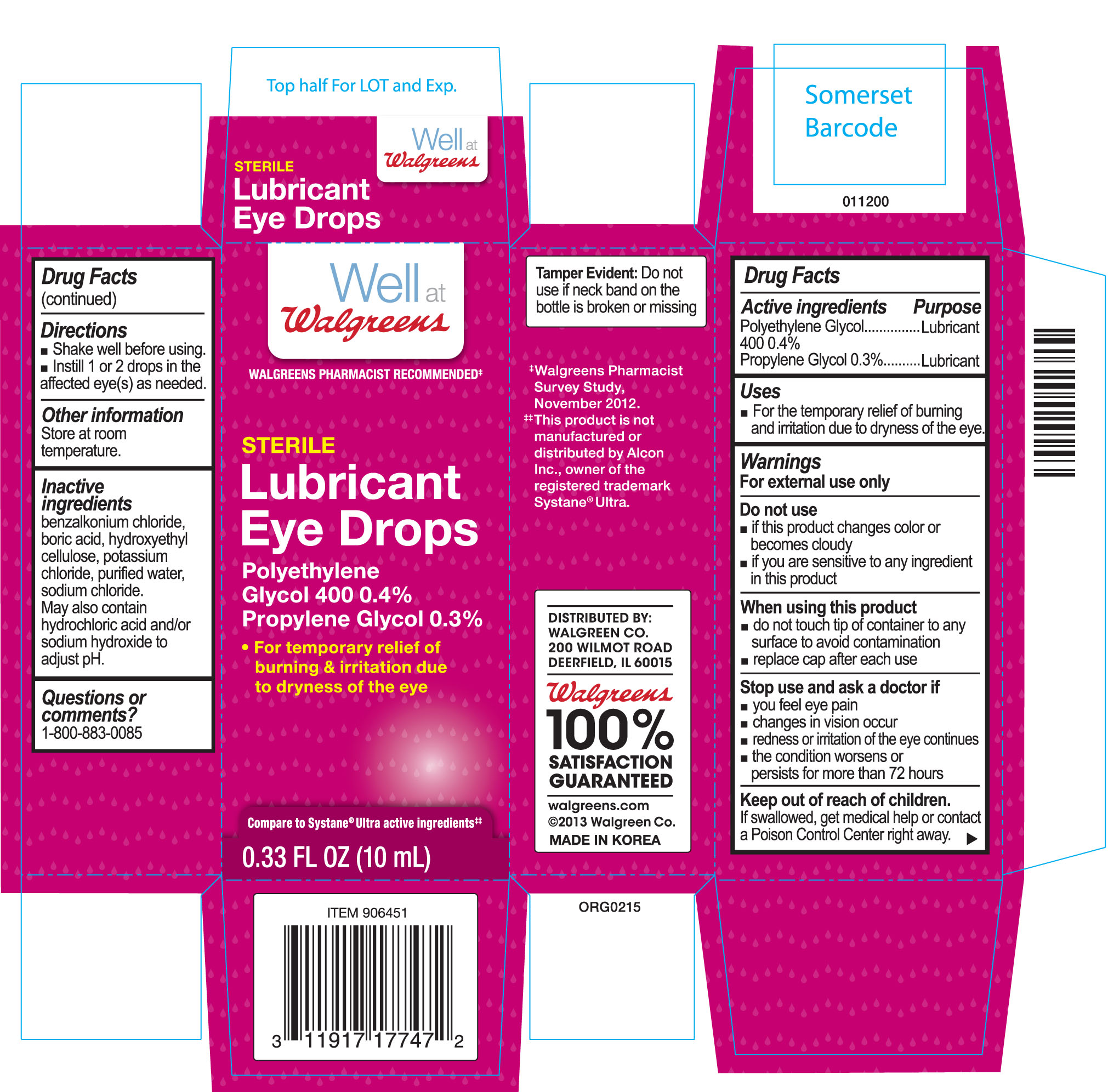 DRUG LABEL: Lubricant Eye
NDC: 0363-6451 | Form: SOLUTION/ DROPS
Manufacturer: Walgreens
Category: otc | Type: HUMAN OTC DRUG LABEL
Date: 20150716

ACTIVE INGREDIENTS: POLYETHYLENE GLYCOL 400 4 mg/1 mL; PROPYLENE GLYCOL 3 mg/1 mL
INACTIVE INGREDIENTS: WATER; SORBITOL; BORIC ACID; SODIUM CHLORIDE; POTASSIUM CHLORIDE; HYDROCHLORIC ACID; SODIUM HYDROXIDE; BENZALKONIUM CHLORIDE

Drug Facts

Active ingredients

Polyethylene Glycol 400 0.4%

Propylene Glycol 0.3%

Purpose

Lubricant

Lubricant

Uses

For the temporary relief of burning and irritation due to dryness of the eye.

Warnings

For external use only.

Do not use

- if this product changes color or becomes cloudy
- if you are sensitive to any ingredient in this product

When using this product

- do not touch tip of container to any surface to avoid contamination
- replace cap after each use

Stop use and ask a doctor if

- you feel eye pain
- changes in vision occur
- redness or irritation of the eye(s) gets worse, persists or lasts more than 72 hours

Keep out of reach of children.

If swallowed, get medical help or contact a Poison Control Center right away.

Directions

- shake well before using
- instill 1 or 2 drops in the affected eye(s) as needed

Other information

Store at room temperature.

Inactive ingredients

benzalkonium chloride, boric acid, hydroxyethyl cellulose, potassium chloride, purified water, sodium chloride. May also contain hydrochloric acid and/or sodium hydroxide to adjust pH.

Questions or comments?

1-800-883-0085

Principal Display Panel Text for Carton Label:

Well at

WALGREENS PHARMACIST RECOMMENDED≠

STERILE

Lubricant

Eye Drops

Polyethylene

Glycol 400 0.4%

Propylene Glycol 0.3%

- For temporary relief of
  burning & irritation due
  to dryness of the eye

Compare to Systane® Ultra active ingredient#

0.3 FL OZ (10 mL)